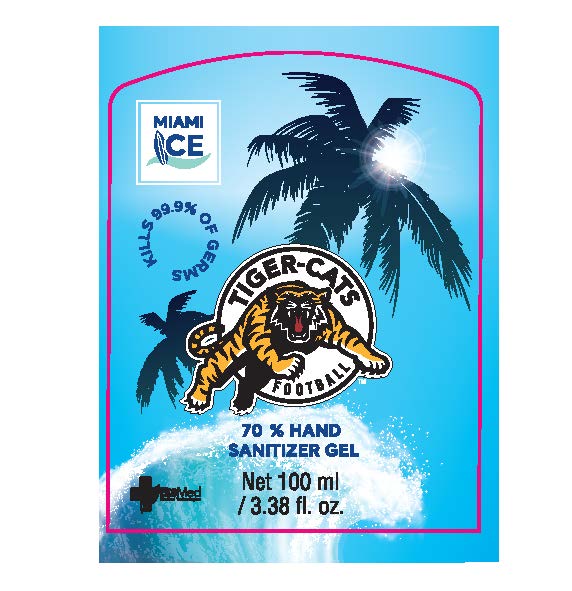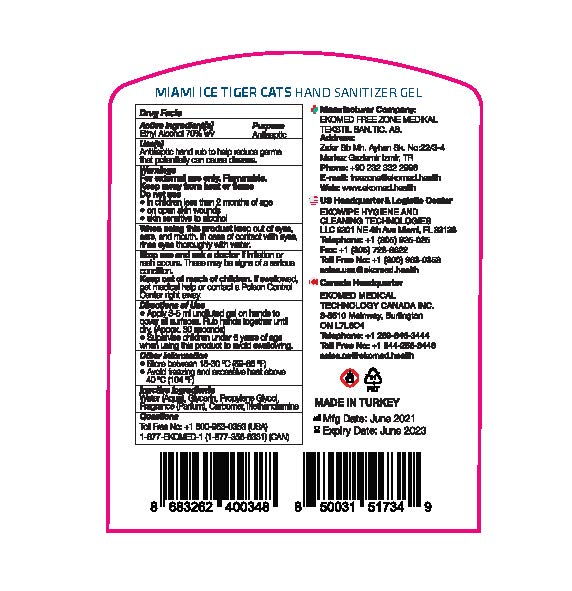 DRUG LABEL: TigerCats 70%
NDC: 81874-008 | Form: GEL
Manufacturer: EKOWIPE HYGIENE AND CLEANING TECHNOLOGIES LLC
Category: otc | Type: HUMAN OTC DRUG LABEL
Date: 20210828

ACTIVE INGREDIENTS: ALCOHOL 70 mL/100 mL
INACTIVE INGREDIENTS: GLYCERIN; PROPYLENE GLYCOL; FRAGRANCE LAVENDER & CHIA F-153480; CARBOMER INTERPOLYMER TYPE A (ALLYL SUCROSE CROSSLINKED); TROLAMINE; WATER

Miami Ice 70% Tiger Cats

Active ingredient

Ethyl alcohol 70%

Purpose

Antiseptic

Uses

- For hand washing to decrease bacteria on the skin
- recommended for repeated use

Warnings

For external use only

Flammable, keep away from fire or flame.

Do not use

in the eyes

Stop use and ask a doctor if

- irritation and redness develop
- condition persists for more than 72 hours

Keep out of reach of children.

If swallowed, get medical help or contact a Poison Control Center right away.

Directions

Wet hands thoroughly with product and allow to dry without wiping

Inactive ingredients

Water, Glycerin, Triethanolamine, Propylene Glycol, Carbomer, Perfum

Questions or comments?

+1 800-963-0353

Package Labeling: TigerCats 70% 100ml

100 ml NDC 81874-008-01